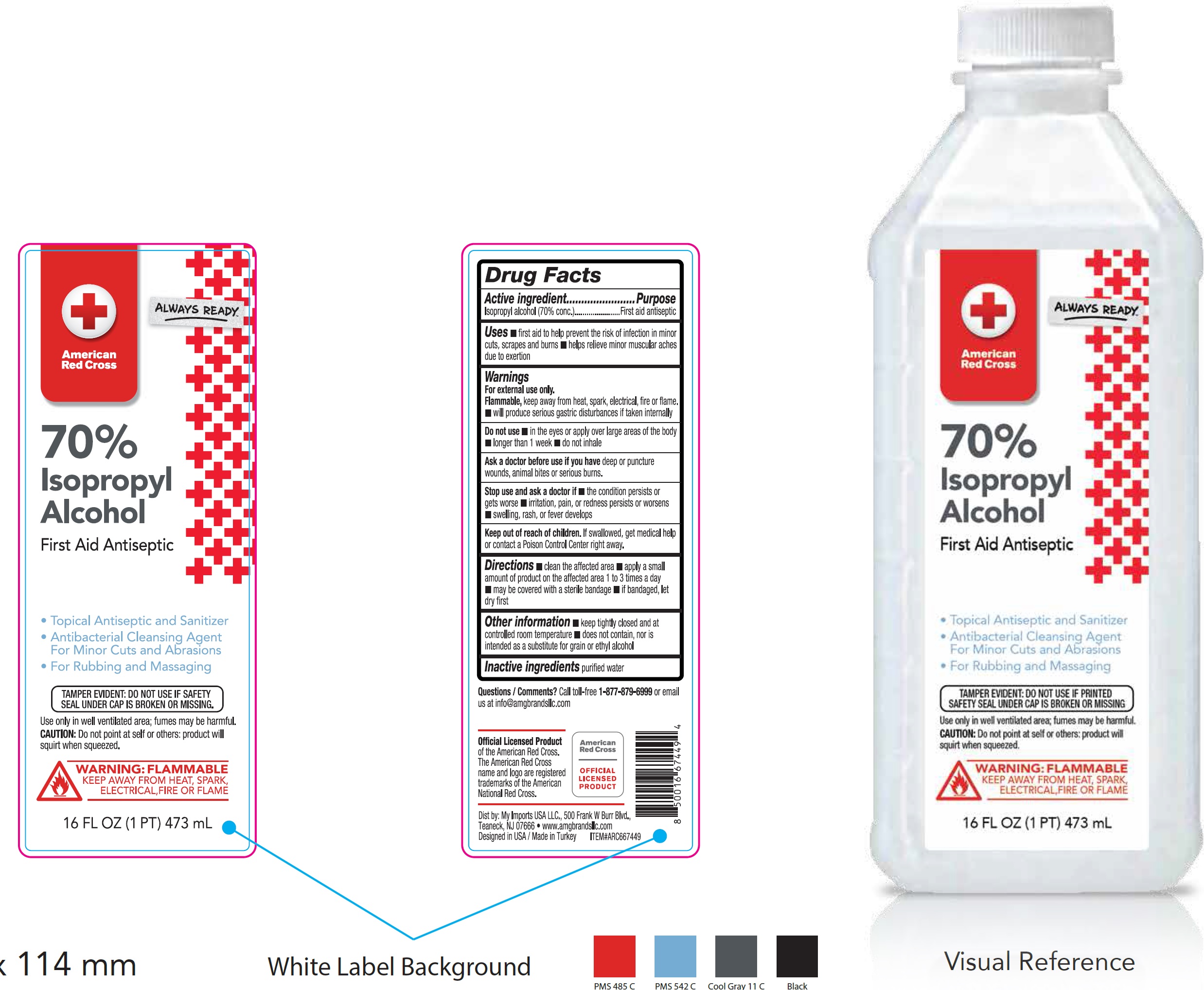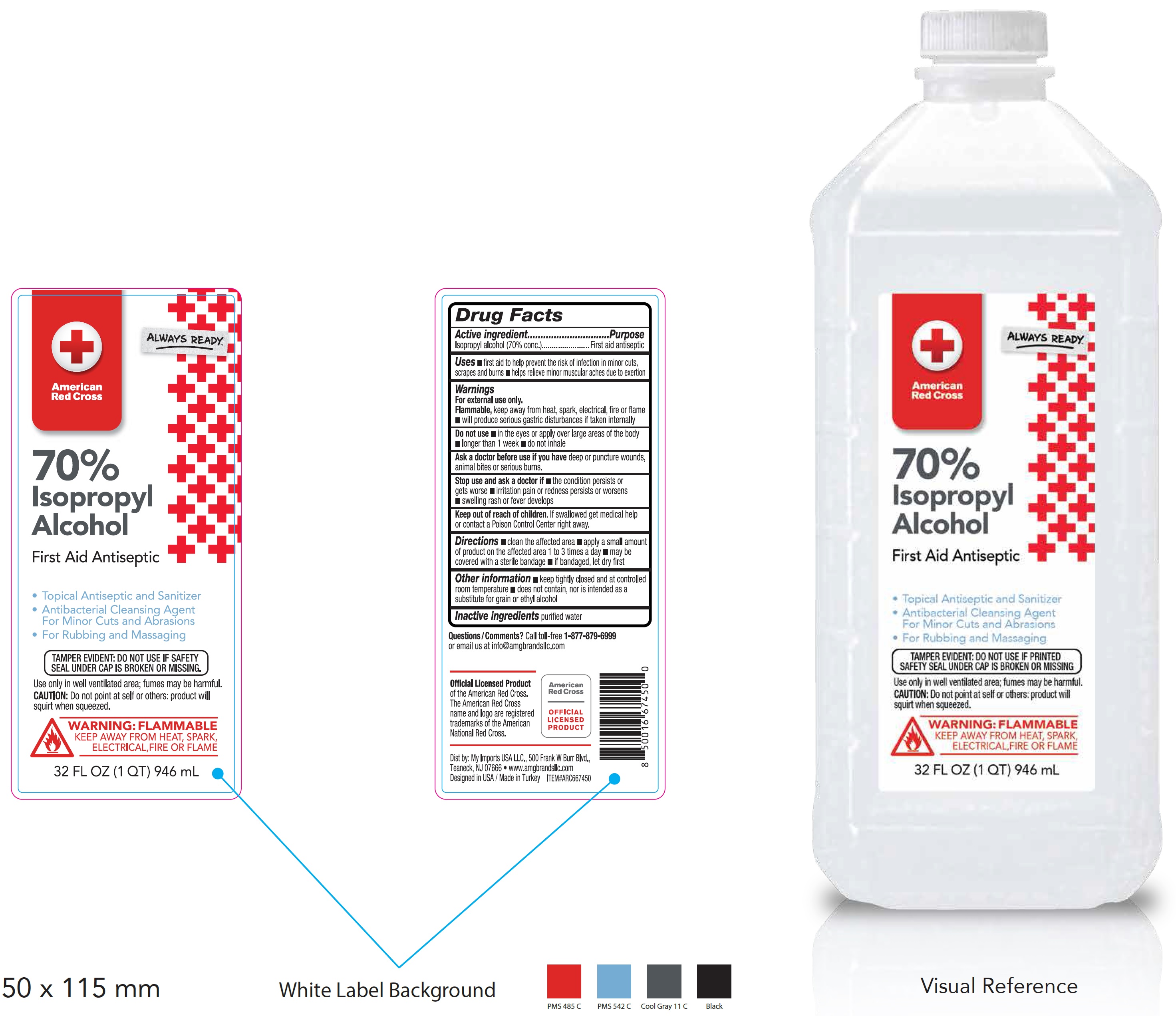 DRUG LABEL: American Red Cross Isopropyl Alcohol First Aid Antiseptic
NDC: 51628-0340 | Form: LIQUID
Manufacturer: My Imports Usa, LLC
Category: otc | Type: HUMAN OTC DRUG LABEL
Date: 20260227

ACTIVE INGREDIENTS: ISOPROPYL ALCOHOL 70 mL/100 mL
INACTIVE INGREDIENTS: WATER

American Red Cross 70% Isopropyl Alcohol First Aid Antiseptic

Active ingredient

Isopropyl alcohol (70% conc.)

Purpose

First aid antiseptic

Uses

• First aid to help prevent the risk of infection in minor cuts, scrapes and burns • helps relieve minor muscular aches due to extertion

Warnings

For external use only.
Flammable,keep away from heat, spark, electrical, fire or flame. • will produce serious gastric disturbances if taken internally

Do not use

• in the eyes or apply over large areas of the body • longer than 1 week • do not inhale

Ask a doctor before use if you have

deep or puncture wounds, animal bites or serious burns.

Stop use and ask a doctor if

• the condition persists or gets worse • irritation, pain or redness persists or worsens • swelling, rash, or fever develops

Keep out of reach of children.

If swallowed, get medical help or contact a Poison Control Center right away.

Directions

• clean the affected area • apply a small amount of product on the affected area 1 to 3 times a day • may be covered with a sterile bandage • if bandaged, let dry first

Other information

• keep tightly closed and at controlled room temperature • does not contain, nor is intended as a substitute for grain or ethyl alcohol

Inactive ingredients

purified water

Questions or Comments?

Call toll-free 1-877-879-6999or email us at info@amgbrandsllc.com